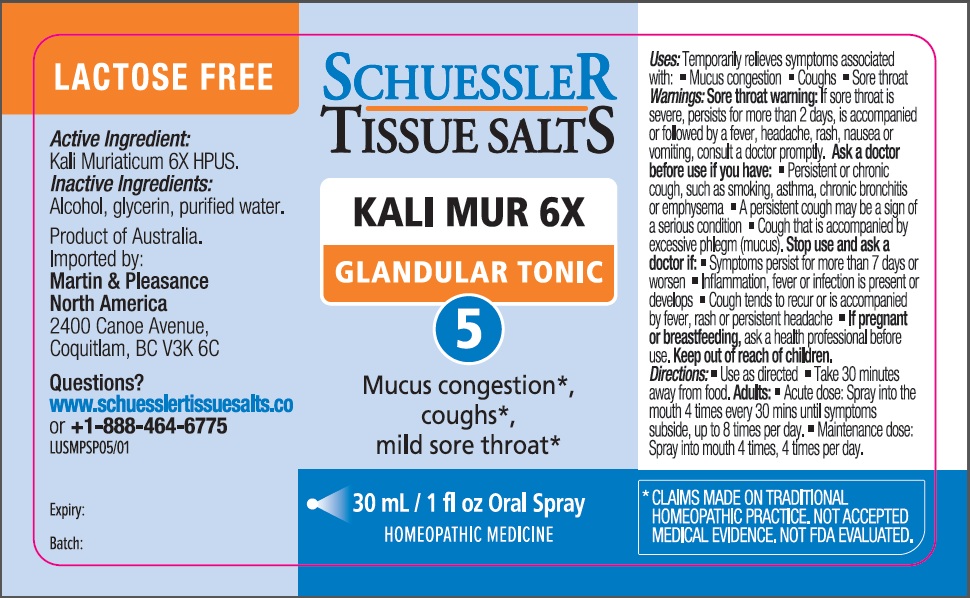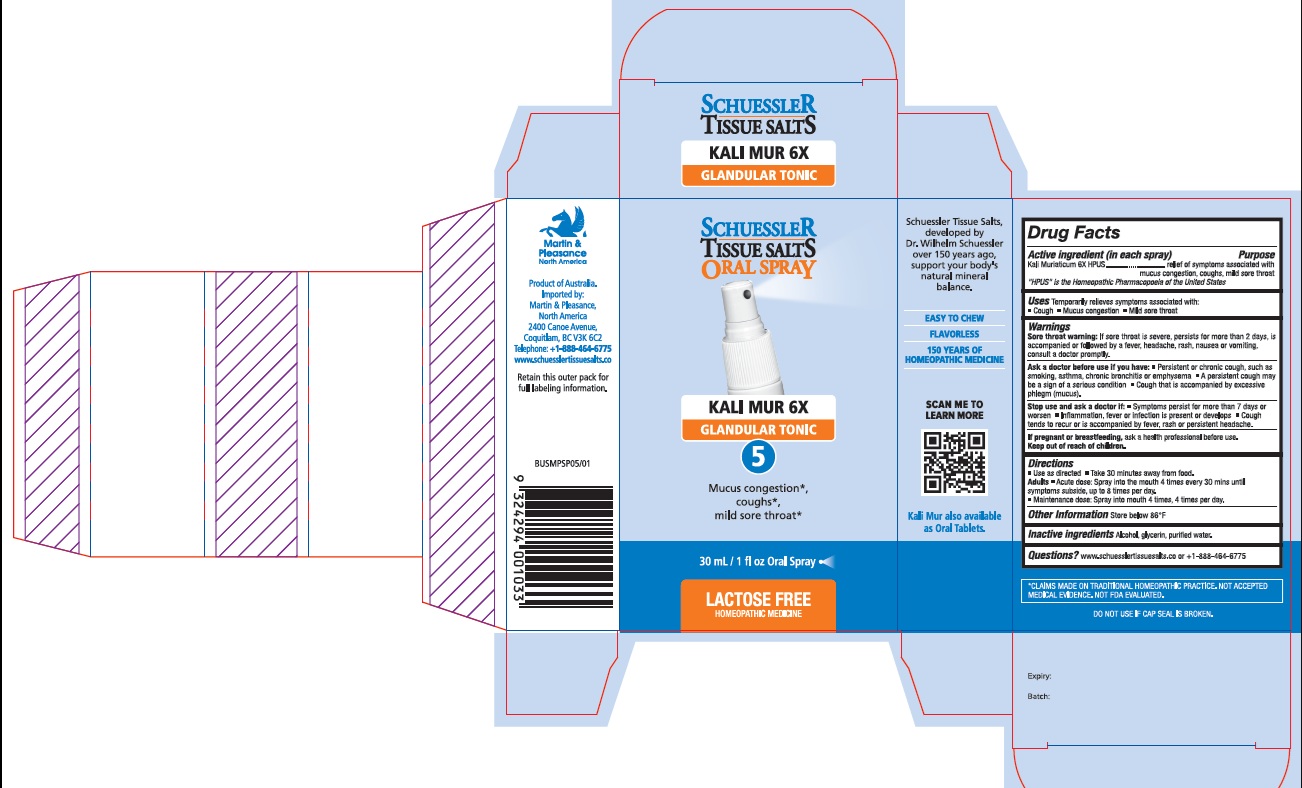 DRUG LABEL: Schuessler Tissue Salts Kali Mur Glandular Tonic 5
NDC: 84999-005 | Form: SPRAY
Manufacturer: Martin & Pleasance Pty Ltd
Category: homeopathic | Type: HUMAN OTC DRUG LABEL
Date: 20250701

ACTIVE INGREDIENTS: POTASSIUM CHLORIDE 6 [hp_X]/30 mL
INACTIVE INGREDIENTS: ALCOHOL; GLYCERIN; WATER

Active ingredient (in each spray) Purpose

Kali Muriaticum 6X HPUS relief of symptoms associated with mucus congestion, coughs, mild sore throat

" HPUS" is the Homeopathic Pharmacopoeia of the United States

Uses

- Temporarily relieves symptoms associated with:
- Mucous congestion
- Cough
- Mild sore throat

Warnings

Sore throat warning: if sore throat is severe, persists for more than 2 days, is accompanied or followed by a fever, headache, rash, nausea or vomiting, consult a doctor promptly.

Ask a doctor before use if you have:

- Persistent or chronic cough, such as smoking, asthma, chronic bronchitis or emphysema
- A persistent cough may be a sign of a serious condition
- Cough that is accompanied by excessive phlegm (mucus).

Stop use and ask a doctor if:

- Symptoms persist for more than 7 days or worsen
- Inflammation, fever or infection is present or develops
- Cough tends to recur or is accompanied by fever, rash or persistent headache.

If pregnant or breastfeeding, ask a health professional before use. Keep out of reach of children.

Directions

- Use as directed
- Take 30 minutes away from food.

Adults

- Acute dose: Spray into the mouth 4 times every 30 mins until symptoms subside, up to 8 times per day.
- Maintenance dose: Spray into mouth 4 times, 4 times per day.

Other lnformation

store below 86°F

Inactive Ingredients

Alcohol , Glycerin, water

Questions?www.schuesslertissuesalts.co or +1-888-464-6775